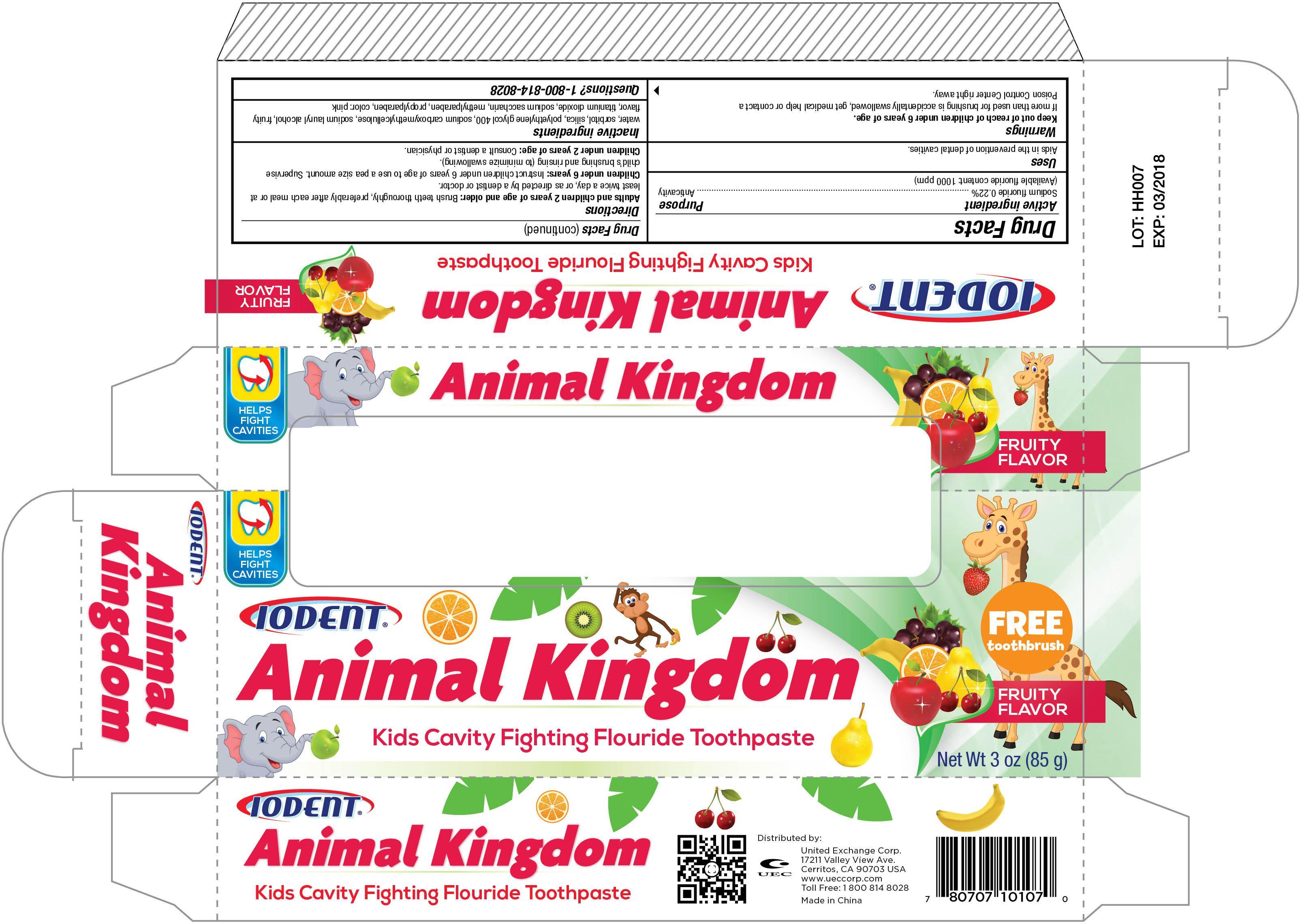 DRUG LABEL: Iodent Animal Kingdom Fruity
NDC: 65923-107 | Form: PASTE
Manufacturer: United Exchange Corp.
Category: otc | Type: HUMAN OTC DRUG LABEL
Date: 20150304

ACTIVE INGREDIENTS: SODIUM FLUORIDE 0.22 g/100 g
INACTIVE INGREDIENTS: WATER; SORBITOL; HYDRATED SILICA; POLYETHYLENE GLYCOL 400; TITANIUM DIOXIDE; SACCHARIN SODIUM; METHYLPARABEN; PROPYLPARABEN

Active Ingredient Purpose

Sodium fluoride 0.22%---------------------------------------------------------------------------------------Anti-Cavity

(Available fluoride content: 1000 ppm)

Uses

Aids in the prevention of dental cavities.

KEEP OUT OF REACH OF CHILDREN

Keep out of the reach of children under 6 years of age.

Warnings

If more than used for brushing is accidentally swallowed, get medical help or contact a Poison Control Center right away.

Directions:

Adults and children 2 years of age and older: Brush teeth thoroughly, preferably after each meal or at least twice a day, or as directed by a dentist or doctor.

Children under 6 years: Instruct children under 6 years of age in good brushing and rinsing habits (to minimize swallowing). Supervise children as necessary until capable of using without supervision.

Children under 2 years of age: Consult a dentist or physician.

Inactive ingredients

water, sorbitol, silica, polyethylene, glycol 400, sodium carboxymethylcellulose, sodium lauryl alcohol, fruity flavor, titanium dioxide, sodium saccharin, methylparaben, propylparaben, color: pink

DOSAGE AND ADMINISTRATION

Distributed by:

United Exchange Corp.

17211 Valley View Ave.,

Cerritos, CA 90703 USA